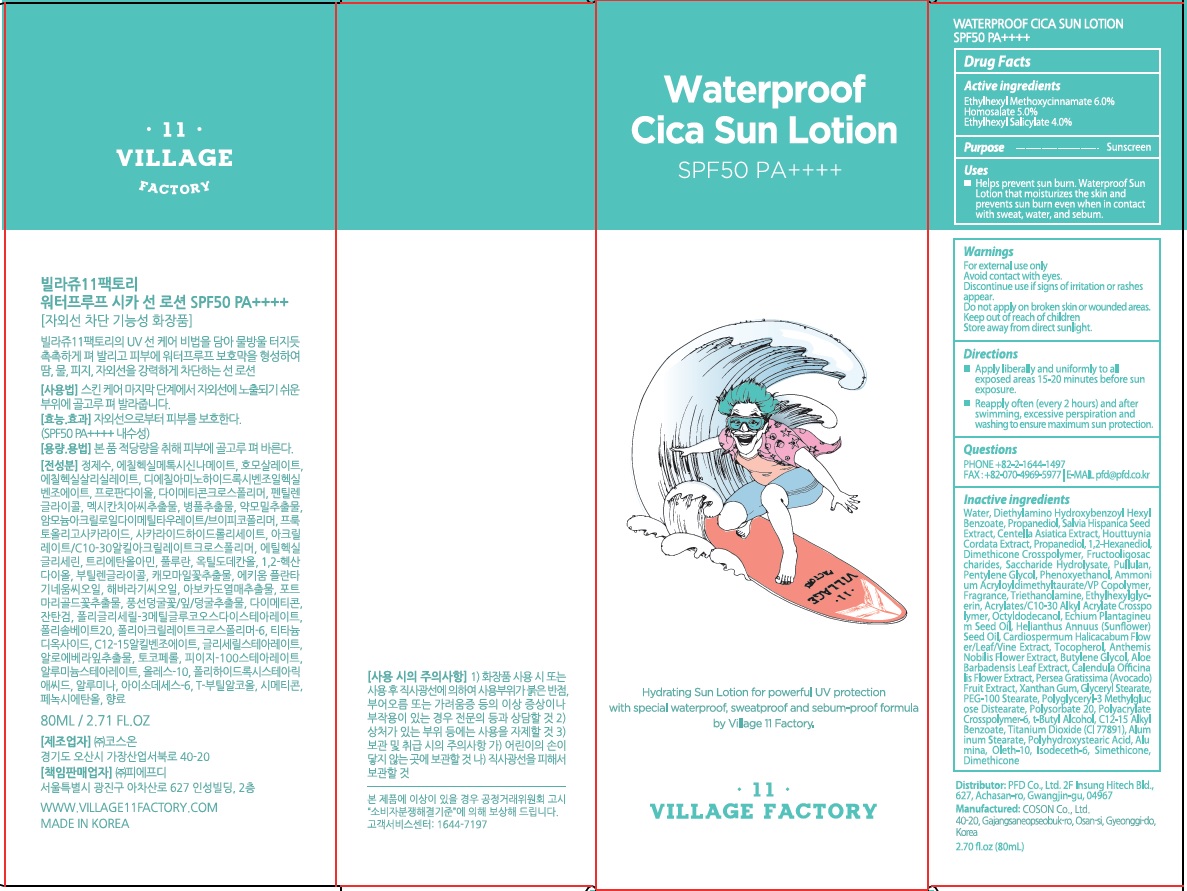 DRUG LABEL: Village11Factory Waterproof Cica Sun
NDC: 72470-040 | Form: LOTION
Manufacturer: PFD Co.,Ltd.
Category: otc | Type: HUMAN OTC DRUG LABEL
Date: 20201201

ACTIVE INGREDIENTS: Octinoxate 6.0 g/80 mL; Homosalate 4.0 g/80 mL; Octisalate 3.2 g/80 mL
INACTIVE INGREDIENTS: Water; Propanediol

ACTIVE INGREDIENTS

Ethylhexyl Methoxycinnamate 6.0%
Homosalate 5.0%
Ethylhexyl Salicylate 4.0%

INACTIVE INGREDIENTS

Water, Diethylamino Hydroxybenzoyl Hexyl Benzoate, Propanediol, Salvia Hispanica Seed Extract, Centella Asiatica Extract, Houttuynia Cordata Extract, Propanediol, 1,2-Hexanediol, Dimethicone Crosspolymer, Fructooligosaccharides, Saccharide Hydrolysate, Pullulan, Pentylene Glycol, Phenoxyethanol, Ammonium Acryloyldimethyltaurate/VP Copolymer, Fragrance, Triethanolamine, Ethylhexylglycerin, Acrylates/C10-30 Alkyl Acrylate Crosspolymer, Octyldodecanol, Echium Plantagineum Seed Oil, Helianthus Annuus (Sunflower) Seed Oil, Cardiospermum Halicacabum Flower/Leaf/Vine Extract, Tocopherol, Anthemis Nobilis Flower Extract, Butylene Glycol, Aloe Barbadensis Leaf Extract, Calendula Officinalis Flower Extract, Persea Gratissima (Avocado) Fruit Extract, Xanthan Gum, Glyceryl Stearate, PEG-100 Stearate, Polyglyceryl-3 Methylglucose Distearate, Polysorbate 20, Polyacrylate Crosspolymer-6, t-Butyl Alcohol, C12-15 Alkyl Benzoate, Titanium Dioxide (CI 77891), Aluminum Stearate, Polyhydroxystearic Acid, Alumina, Oleth-10, Isodeceth-6, Simethicone, Dimethicone

PURPOSE

Sunscreen

WARNINGS

For external use only
Avoid contact with eyes.
Discontinue use if signs of irritation or rashes appear.
Do not apply on broken skin or wounded areas.
Keep out of reach of children
Store away from direct sunlight.

DESCRIPTION

Uses:

■ Helps prevent sun burn. Waterproof Sun Lotion that moisturizes the skin and prevents sun burn even when in contact with sweat, water, and sebum.

Directions:

■ Apply liberally and uniformly to all exposed areas 15-20 minutes before sun exposure.
■ Reapply often (every 2 hours) and after swimming, excessive perspiration and washing to ensure maximum sun protection.